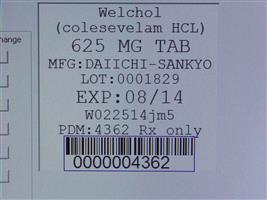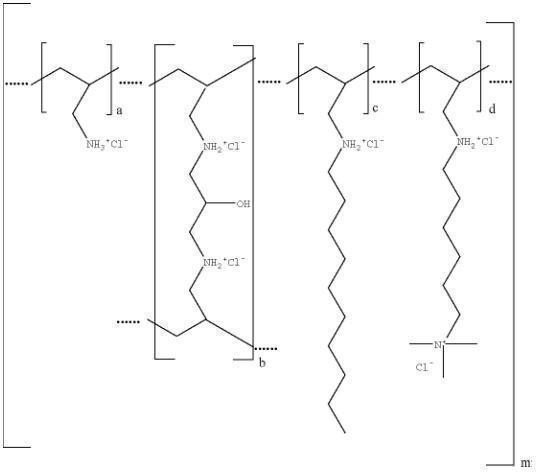 DRUG LABEL: Welchol
NDC: 68151-4362 | Form: TABLET, FILM COATED
Manufacturer: Carilion Materials Management
Category: prescription | Type: HUMAN PRESCRIPTION DRUG LABEL
Date: 20160806

ACTIVE INGREDIENTS: COLESEVELAM HYDROCHLORIDE 625 mg/1 1

HIGHLIGHTS OF PRESCRIBING INFORMATION

These highlights do not include all the information needed to use WELCHOL safely and effectively. See full prescribing information for WELCHOL.
WELCHOL (colesevelam hydrochloride)
Initial U.S. Approval: 2000

RECENT MAJOR CHANGES

Warnings and Precautions (5.6) 5/2013

1 INDICATIONS AND USAGE

WELCHOL is a bile acid sequestrant indicated as an adjunct to diet and exercise to

- reduce elevated low-density lipoprotein cholesterol (LDL-C) in adults with primary hyperlipidemia as monotherapy or in combination with a hydroxymethyl-glutaryl-coenzyme A (HMG CoA) reductase inhibitor (statin) (1.1).
- reduce LDL-C levels in boys and postmenarchal girls, 10 to 17 years of age, with heterozygous familial hypercholesterolemia as monotherapy or in combination with a statin after failing an adequate trial of diet therapy.
- improve glycemic control in adults with type 2 diabetes mellitus (1.2).

Important Limitations of Use (1.3):

- Do not use for glycemic control in type 1 diabetes or for treating diabetic ketoacidosis.
- WELCHOL has not been studied in type 2 diabetes in combination with a dipeptidyl peptidase 4 inhibitor.
- WELCHOL has not been studied in Fredrickson Type I, III, IV, and V dyslipidemias.
- WELCHOL has not been studied in children younger than 10 years of age or in pre-menarchal girls.

2 DOSAGE AND ADMINISTRATION

- WELCHOL Tablets: The recommended dose is 6 tablets once daily or 3 tablets twice daily. WELCHOL Tablets should be taken with a meal and liquid (2.1, 2.2).
- WELCHOL for Oral Suspension: The recommended dose is one 3.75 gram packet once daily or one 1.875 gram packet twice daily. To prepare, empty the entire contents of one packet into a glass or cup. Add ½ to 1 cup (4 to 8 ounces) of water, fruit juice, or diet soft drinks. Stir well and drink. WELCHOL for Oral Suspension should be taken with meals. To avoid esophageal distress, WELCHOL for Oral Suspension should not be taken in its dry form (2.1, 2.2).

3 DOSAGE FORMS AND STRENGTHS

Tablets: 625 mg (3)

Oral suspension: 3.75 gram packet, 1.875 gram packet (3)

4 CONTRAINDICATIONS

- Do not use in patients with a history of bowel obstruction (4)
- Do not use in patients with serum triglyceride (TG) concentrations >500 mg/dL (4)
- Do not use in patients with a history of hypertriglyceridemia-induced pancreatitis (4)

5 WARNINGS AND PRECAUTIONS

- The effect of WELCHOL on cardiovascular morbidity and mortality has not been determined (5.1).
- WELCHOL can increase TG, particularly when used with insulin or sulfonylureas. Marked hypertriglyceridemia can cause acute pancreatitis. The effect of hypertriglyceridemia on the risk of coronary artery disease is uncertain. Monitor lipids, including TG and non-high density lipoprotein cholesterol (non-HDL-C) (5.2).
- Bile acid sequestrants may decrease absorption of fat-soluble vitamins. Use caution in patients susceptible to fat-soluble vitamin deficiencies (5.3).
- Because of its constipating effects, WELCHOL is not recommended in patients at risk of bowel obstruction (e.g., patients with gastroparesis, other gastrointestinal motility disorders or a history of major gastrointestinal surgery) (5.4).
- WELCHOL reduces gastrointestinal absorption of some drugs. Administer drugs with a known interaction with colesevelam at least 4 hours prior to WELCHOL. Drugs that have not been tested for interaction with colesevelam, especially those with a narrow therapeutic index, should also be administered at least 4 hours prior to WELCHOL. Alternatively, monitor drug levels of the co-administered drug (5.5, 7, 12.3).
- WELCHOL for Oral Suspension contains 13.5 mg phenylalanine per 1.875 gram packet and 27 mg phenylalanine per 3.75 gram packet (5.6, 11).

6 ADVERSE REACTIONS

In clinical trials, the most common (incidence ≥2% and greater than placebo) adverse reactions with WELCHOL included constipation, dyspepsia, and nausea.

Postmarketing reports with concomitant WELCHOL administration include:

- Increased seizure activity or decreased phenytoin levels in patients receiving phenytoin. Administer phenytoin 4 hours prior to WELCHOL.
- Reduced International Normalized Ratio (INR) in patients receiving warfarin. Monitor INR.
- Elevated thyroid-stimulating hormone (TSH) in patients receiving thyroid hormone replacement therapy. Administer thyroid hormones 4 hours prior to WELCHOL.

Other postmarketing reports include bowel obstruction, dysphagia, esophageal obstruction, fecal impaction, hypertriglyceridemia, pancreatitis, and increased transaminases (5.5, 6.2, 7, 12.3).

To report SUSPECTED ADVERSE REACTIONS, contact Daiichi Sankyo, Inc. at 1-877-437-7763 or FDA at 1-800-332-1088 or www.fda.gov/medwatch.

7 DRUG INTERACTIONS

In drug interaction studies, WELCHOL reduced levels of cyclosporine, glimepiride, glipizide, glyburide, levothyroxine, olmesartan medoxomil, and oral contraceptives containing ethinyl estradiol and norethindrone. WELCHOL increased levels of metformin when coadministered with metformin extended release. There have been postmarketing reports of decreases in phenytoin levels in patients receiving phenytoin concomitantly with WELCHOL and decreases in INR in patients receiving warfarin concomitantly with WELCHOL (5.5, 7, 12.3).

FULL PRESCRIBING INFORMATION

1 INDICATIONS AND USAGE

1.1 Primary Hyperlipidemia

WELCHOL is indicated as an adjunct to diet and exercise to reduce elevated low-density lipoprotein cholesterol (LDL-C) in adults with primary hyperlipidemia (Fredrickson Type IIa) as monotherapy or in combination with a hydroxymethyl-glutaryl-coenzyme A (HMG CoA) reductase inhibitor (statin).

WELCHOL is indicated as monotherapy or in combination with a statin to reduce LDL-C levels in boys and postmenarchal girls, 10 to 17 years of age, with heterozygous familial hypercholesterolemia if after an adequate trial of diet therapy the following findings are present:

a. LDL-C remains ≥ 190 mg/dL or
b. LDL-C remains ≥ 160 mg/dL and

- there is a positive family history of premature cardiovascular disease or
- two or more other CVD risk factors are present in the pediatric patient.

Lipid-altering agents should be used in addition to a diet restricted in saturated fat and cholesterol when response to diet and non-pharmacological interventions alone has been inadequate [See Clinical Studies (14.1)].

In patients with coronary heart disease (CHD) or CHD risk equivalents such as diabetes mellitus, LDL-C treatment goals are < 100 mg/dL. An LDL-C goal of < 70 mg/dL is a therapeutic option on the basis of recent trial evidence. If LDL-C is at goal but the serum triglyceride (TG) value is > 200 mg/dL, then non-HDL cholesterol (non-HDL-C) (total cholesterol [TC] minus high density lipoprotein cholesterol [HDL-C]) becomes a secondary target of therapy. The goal for non-HDL-C in persons with high serum TG is set at 30 mg/dL higher than that for LDL-C.

1.2 Type 2 Diabetes Mellitus

WELCHOL is indicated as an adjunct to diet and exercise to improve glycemic control in adults with type 2 diabetes mellitus [See Clinical Studies (14.2)].

Diabetes mellitus is considered a CHD risk equivalent. In addition to glycemic control, intensive lipid control is warranted [See Indications and Usage (1.1) and Warnings and Precautions (5.2)].

1.3 Important Limitations of Use

- WELCHOL should not be used for the treatment of type 1 diabetes or for the treatment of diabetic ketoacidosis.
- WELCHOL has not been studied in type 2 diabetes in combination with a dipeptidyl peptidase 4 inhibitor.
- WELCHOL has not been studied in pediatric patients with type 2 diabetes.
- WELCHOL has not been studied in Fredrickson Type I, III, IV, and V dyslipidemias.
- WELCHOL has not been studied in children younger than 10 years of age or in pre-menarchal girls.

2 DOSAGE AND ADMINISTRATION

2.1 Primary Hyperlipidemia

The recommended dose of WELCHOL Tablets in adults, whether used as monotherapy or in combination with a statin, is 6 tablets once daily or 3 tablets twice daily. WELCHOL Tablets should be taken with a meal and liquid.

The recommended dose of WELCHOL for Oral Suspension, in adults and children 10 to 17 years of age, is one 3.75 gram packet once daily or one 1.875 gram packet twice daily. To prepare, empty the entire contents of one packet into a glass or cup. Add ½ to 1 cup (4 to 8 ounces) of water, fruit juice, or diet soft drinks. Stir well and drink. WELCHOL for Oral Suspension should be taken with meals. To avoid esophageal distress, WELCHOL for Oral Suspension should not be taken in its dry form. Due to tablet size, it is recommended that any patient who has difficulty swallowing tablets use WELCHOL for Oral Suspension.

WELCHOL can be dosed at the same time as a statin or the two drugs can be dosed apart [See Clinical Studies (14.1)].

After initiation of WELCHOL, lipid levels should be analyzed within 4 to 6 weeks.

2.2 Type 2 Diabetes Mellitus

The recommended dose of WELCHOL Tablets is 6 tablets once daily or 3 tablets twice daily. WELCHOL should be taken with a meal and liquid.

The recommended dose of WELCHOL for Oral Suspension is one 3.75 gram packet once daily or one 1.875 gram packet twice daily. To prepare, empty the entire contents of one packet into a glass or cup. Add ½ to 1 cup (4 to 8 ounces) of water, fruit juice, or diet soft drinks. Stir well and drink. WELCHOL for Oral Suspension should be taken with meals. To avoid esophageal distress, WELCHOL for Oral Suspension should not be taken in its dry form.

3 DOSAGE FORMS AND STRENGTHS

- Tablets: 625 mg tablets are off-white, oval, film-coated and imprinted with “Sankyo” and “C01” on one side.
- Oral Suspension: a white to pale yellow powder containing yellow granules packaged in single-dose packets: 3.75 gram single-dose packet, 1.875 gram single-dose packet.

4 CONTRAINDICATIONS

WELCHOL is contraindicated in patients with

- A history of bowel obstruction [See Warnings and Precautions (5.4)]
- Serum TG concentrations >500 mg/dL [See Warnings and Precautions (5.2)]
- A history of hypertriglyceridemia-induced pancreatitis [See Warnings and Precautions (5.2)]

5 WARNINGS AND PRECAUTIONS

5.1 General

The effect of WELCHOL on cardiovascular morbidity and mortality has not been determined.

5.2 Serum Triglycerides

WELCHOL, like other bile acid sequestrants, can increase serum TG concentrations.

WELCHOL had small effects on serum TG (median increase 5% compared to placebo) in trials of patients with primary hyperlipidemia [See Adverse Reactions (6.1) and Clinical Studies (14.1)].

In clinical trials in patients with type 2 diabetes, greater increases in TG levels occurred when WELCHOL was used as monotherapy (median increase 9.7% compared to placebo) and when WELCHOL was used in combination with pioglitazone (median increase 11% compared to placebo in combination with pioglitazone), sulfonylureas (median increase 18% compared to placebo in combination with sulfonylureas), and insulin (median increase 22% compared to placebo in combination with insulin) [See Adverse Reactions (6.1) and Clinical Studies (14.2)]. Hypertriglyceridemia of sufficient severity can cause acute pancreatitis. The long-term effect of hypertriglyceridemia on the risk of coronary artery disease is uncertain. In patients with type 2 diabetes, the effect of WELCHOL on LDL-C levels may be attenuated by WELCHOL’s effects on TG levels and a smaller reduction in non HDL-C compared to the reduction in LDL-C. Caution should be exercised when treating patients with TG levels greater than 300 mg/dL. Because most patients in the WELCHOL clinical trials had baseline TG <300 mg/dL, it is unknown whether patients with more uncontrolled baseline hypertriglyceridemia would have greater increases in serum TG levels with WELCHOL. In addition, the use of WELCHOL is contraindicated in patients with TG levels >500 mg/dL [See Contraindications (4)]. Lipid parameters, including TG levels and non-HDL-C, should be obtained before starting WELCHOL and periodically thereafter. WELCHOL should be discontinued if TG levels exceed 500 mg/dL or if the patient develops hypertriglyceridemia-induced pancreatitis [See Adverse Reactions (6.1)].

5.3 Vitamin K or Fat-Soluble Vitamin Deficiencies Precautions

Bile acid sequestrants may decrease the absorption of fat-soluble vitamins A, D, E, and K. No specific clinical studies have been conducted to evaluate the effects of WELCHOL on the absorption of co-administered dietary or supplemental vitamin therapy. In non-clinical safety studies, rats administered colesevelam hydrochloride at doses greater than 30-fold the projected human clinical dose experienced hemorrhage from vitamin K deficiency. Patients on oral vitamin supplementation should take their vitamins at least 4 hours prior to WELCHOL. Caution should be exercised when treating patients with a susceptibility to deficiencies of vitamin K (e.g., patients on warfarin, patients with malabsorption syndromes) or other fat-soluble vitamins.

5.4 Gastrointestinal Disorders

Because of its constipating effects, WELCHOL is not recommended in patients with gastroparesis, other gastrointestinal motility disorders, and in those who have had major gastrointestinal tract surgery and who may be at risk for bowel obstruction. Because of the tablet size, WELCHOL Tablets can cause dysphagia or esophageal obstruction and should be used with caution in patients with dysphagia or swallowing disorders. To avoid esophageal distress, WELCHOL for Oral Suspension should not be taken in its dry form. Always mix WELCHOL for Oral Suspension with water, fruit juice, or diet soft drinks before ingesting.

5.5 Drug Interactions

WELCHOL reduces gastrointestinal absorption of some drugs. Drugs with a known interaction with colesevelam should be administered at least 4 hours prior to WELCHOL. Drugs that have not been tested for interaction with colesevelam, especially those with a narrow therapeutic index, should also be administered at least 4 hours prior to WELCHOL. Alternatively, the physician should monitor drug levels of the co-administered drug [See Drug Interactions (7) and Clinical Pharmacology (12.3)].

5.6 Phenylketonurics

WELCHOL for Oral Suspension contains 13.5 mg phenylalanine per 1.875 gram packet and 27 mg phenylalanine per 3.75 gram packet [See Description (11)].

5.7 Macrovascular Outcomes

There have been no clinical studies establishing conclusive evidence of macrovascular disease risk reduction with WELCHOL or any other antidiabetic drugs.

6 ADVERSE REACTIONS

6.1 Clinical Studies Experience

Because clinical studies are conducted under widely varying conditions, adverse reaction rates observed in the clinical studies of a drug cannot be directly compared to rates in clinical studies of another drug and may not reflect the rates observed in practice.

Primary Hyperlipidemia: In 7 double-blind, placebo-controlled, clinical trials, 807 patients with primary hyperlipidemia (age range 18-86 years, 50% women, 90% Caucasians, 7% Blacks, 2% Hispanics, 1% Asians) and elevated LDL-C were treated with WELCHOL 1.5 g/day to 4.5 g/day from 4 to 24 weeks (total exposure 199 patient-years).

In clinical trials for the reduction of LDL-C, 68% of patients receiving WELCHOL vs. 64% of patients receiving placebo reported an adverse reaction.

Table 1 Placebo-Controlled Clinical Studies of WELCHOL for Primary Hyperlipidemia: Adverse Reactions Reported in ≥ 2% of Patients and More Commonly than in Patients Given Placebo, Regardless of Investigator Assessment of Causality
 | Number of Patients (%)
 | WELCHOL N = 807 | Placebo N = 258
Constipation | 89 (11.0) | 18 (7.0)
Dyspepsia | 67 (8.3) | 9 (3.5)
Nausea | 34 (4.2) | 10 (3.9)
Accidental injury | 30 (3.7) | 7 (2.7)
Asthenia | 29 (3.6) | 5 (1.9)
Pharyngitis | 26 (3.2) | 5 (1.9)
Flu syndrome | 26 (3.2) | 8 (3.1)
Rhinitis | 26 (3.2) | 8 (3.1)
Myalgia | 17 (2.1) | 1 (0.4)

Pediatric Patients 10 to 17 Years of Age: In an 8-week double-blind, placebo-controlled study boys and post menarchal girls, 10 to 17 years of age, with heterozygous familial hypercholesterolemia (heFH) (n=192), were treated with WELCHOL tablets (1.9-3.8 g, daily) or placebo tablets [See Clinical Studies (14.1)].

Table 2 Placebo-Controlled Clinical Study of WELCHOL for Primary Hyperlipidemia in heFH Pediatric Patients: Adverse Reactions Reported in ≥2% of Patients and More Commonly than in Patients Given Placebo, Regardless of Investigator Assessment of Causality
 | Number of Patients (%)
 | WELCHOL N = 129 | Placebo N = 65
Nasopharyngitis | 8 (6.2) | 3 (4.6)
Headache | 5 (3.9) | 2 (3.1)
Fatigue | 5 (3.9) | 1 (1.5)
Creatine Phosphokinase Increase | 3 (2.3) | 0 (0.0)
Rhinitis | 3 (2.3) | 0 (0.0)
Vomiting | 3 (2.3) | 1 (1.5)

The reported adverse reactions during the additional 18-week open-label treatment period with WELCHOL 3.8 g per day were similar to those during the double-blind period and included headache (7.6%), nasopharyngitis (5.4%), upper respiratory tract infection (4.9%), influenza (3.8%), and nausea (3.8%) [See Clinical Studies (14.1)].

Type 2 Diabetes Mellitus: The safety of WELCHOL in patients with type 2 diabetes mellitus was evaluated in 5 add-on combination and 1 monotherapy double-blind, 12-26 week, placebo-controlled clinical trials [see Clinical Studies (14.2)]. In these studies 1022 patients were exposed to WELCHOL. The mean exposure duration was 20 weeks (total exposure 393 patient-years). Patients were to receive 3.8 grams of WELCHOL per day. The mean age of patients exposed to WELCHOL was 55.7 years, 52.8 percent of the population was male and 61.9% were Caucasian, 4.8% were Asian, and 15.9% were Black or African American. At baseline the population had a mean HbA1C of 8.2% and 26% had past medical history suggestive of microvascular complications of diabetes. Baseline characteristics in the placebo group were comparable.

In clinical trials of type 2 diabetes, 57% of patients receiving WELCHOL vs. 52% of patients receiving placebo reported an adverse reaction.

Table 3 shows common adverse reactions associated with the use of WELCHOL in the 1015 patients with type 2 diabetes. These adverse reactions were not present at baseline, occurred more commonly on WELCHOL than on placebo, and occurred in at least 2% of patients treated with WELCHOL.

Table 3 Placebo-Controlled Clinical Studies of WELCHOL for Type 2 Diabetes: Adverse Reactions Reported in ≥ 2% of Patients and More Commonly than in Patients Given Placebo, Regardless of Investigator Assessment of Causality
 | Number of Patients (%)
 | WELCHOL N = 1015 | Placebo N = 1010
Constipation | 66 (6.5) | 22 (2.2)
Hypoglycemia | 35 (3.4) | 31 (3.1)
Dyspepsia | 28 (2.8) | 10 (1.0)
Nausea | 26 (2.6) | 16 (1.6)
Hypertension | 26 (2.6) | 19 (1.9)
Back Pain | 23 (2.3) | 13 (1.3)

A total of 5.3% of WELCHOL-treated patients and 3.6% of placebo-treated patients were discontinued from the diabetes trials due to adverse reactions. This difference was driven mostly by gastrointestinal adverse reactions such as abdominal pain and constipation.

One patient in the add-on to sulfonylurea trial discontinued due to body rash and mouth blistering that occurred on the first day of dosing of WELCHOL, which may represent a hypersensitivity reaction to WELCHOL.

Hypertriglyceridemia: Patients with fasting serum TG levels above 500 mg/dL were excluded from the diabetes clinical trials. In the diabetes trials, 1292 (67.7%) patients had baseline fasting serum TG levels less than 200 mg/dL, 426 (22.3%) had baseline fasting serum TG levels between 200 and less than 300 mg/dL, 175 (9.2%) had baseline fasting serum TG levels between 300 and 500 mg/dL, and 16 (0.8%) had fasting serum TG levels greater than or equal to 500 mg/dL. The median baseline fasting TG concentration for the study population was 160 mg/dL; the median post-treatment fasting TG was 180 mg/dL in the WELCHOL group and 162 mg/dL in the placebo group. WELCHOL therapy resulted in a median placebo-corrected increase in serum TG of 9.7% (p=0.03) in the monotherapy study and of 5% (p=0.22), 11% (p<0.001), 18% (p<0.001), and 22% (p<0.001), when added to metformin, pioglitazone, sulfonylureas, and insulin, respectively [See Warnings and Precautions (5.2) and Clinical Studies (14.2)]. In comparison, WELCHOL resulted in a median increase in serum TG of 5% compared to placebo (p=0.42) in a 24-week monotherapy lipid-lowering trial [See Clinical Studies (14.1)].

Treatment-emergent fasting TG concentrations ≥500 mg/dL occurred in 0.9% of WELCHOL-treated patients compared to 0.7% of placebo-treated patients in the diabetes trials. Among these patients, the TG concentrations with WELCHOL (median 606 mg/dL; interquartile range 570-794 mg/dL) were similar to that observed with placebo (median 663 mg/dL; interquartile range 542-984 mg/dL). Five (0.6%) patients on WELCHOL and 3 (0.3%) patients on placebo developed TG elevations ≥1000 mg/dL. In all WELCHOL clinical trials, including studies in patients with type 2 diabetes and patients with primary hyperlipidemia, there were no reported cases of acute pancreatitis associated with hypertriglyceridemia. It is unknown whether patients with more uncontrolled, baseline hypertriglyceridemia would have greater increases in serum TG levels with WELCHOL [See Contraindications (4) and Warnings and Precautions (5.2)].

Cardiovascular adverse events: During the diabetes clinical trials, the incidence of patients with treatment-emergent serious adverse events involving the cardiovascular system was 2.2% (22/1015) in the WELCHOL group and 1% (10/1010) in the placebo group. These overall rates included disparate events (e.g., myocardial infarction, aortic stenosis, and bradycardia); therefore, the significance of this imbalance is unknown.

6.2 Post-marketing Experience

The following additional adverse reactions have been identified during post-approval use of WELCHOL. Because these reactions are reported voluntarily from a population of uncertain size, it is generally not possible to reliably estimate their frequency or establish a causal relationship to drug exposure.

Drug Interactions with concomitant WELCHOL administration include:
  - Increased seizure activity or decreased phenytoin levels in patients receiving phenytoin. Phenytoin should be administered 4 hours prior to WELCHOL.
  - Reduced International Normalized Ratio (INR) in patients receiving warfarin therapy. In warfarin-treated patients, INR should be monitored frequently during WELCHOL initiation then periodically thereafter.
  - Elevated thyroid-stimulating hormone (TSH) in patients receiving thyroid hormone replacement therapy. Thyroid hormone replacement should be administered 4 hours prior to WELCHOL [See Drug Interactions (7)].
Gastrointestinal Adverse Reactions
  Bowel obstruction (in patients with a history of bowel obstruction or resection), dysphagia (tablet and oral suspension formulations) or esophageal obstruction (occasionally requiring medical intervention), fecal impaction, pancreatitis, abdominal distension, exacerbation of hemorrhoids, and increased transaminases.
Laboratory Abnormalities
  Hypertriglyceridemia

7 DRUG INTERACTIONS

Table 4 lists the drugs that have been tested in in vitro binding, in vivo drug interaction studies with colesevelam and/or drugs with postmarketing reports consistent with potential drug-drug interactions. Orally administered drugs that have not been tested for interaction with colesevelam, especially those with a narrow therapeutic index, should also be administered at least 4 hours prior to WELCHOL. Alternatively, the physician should monitor drug levels of the co-administered drug.

Table 4 Drugs Tested in In Vitro Binding or In Vivo Drug Interaction Testing or With Post-Marketing Reports
Drugs with a known interaction with colesevelam: Decrease in exposure of coadministered drug | cyclosporinec, glimepiridea, glipizidea, glyburidea, levothyroxinea, olmesartan medoxomila, and oral contraceptives containing ethinyl estradiol and norethindronea
Drugs with a known interaction with colesevelam: Increase in exposure of coadministered drug | metformin extended release (ER)d
Drug(s) with postmarketing reports consistent with potential drug-drug interactions when coadministered with WELCHOL | phenytoina, warfarinb
Drugs that do not interact with colesevelam based on in vitro or in vivo testing | aspirin, atenolol, cephalexin, ciprofloxacin, digoxin, enalapril, fenofibrate, lovastatin, metformin, metoprolol, phenytoina, pioglitazone, rosiglitazone, quinidine, repaglinide, sitagliptin, valproic acid, verapamil, warfarinb
a Should be administered at least 4 hours prior to WELCHOL
b No significant alteration of warfarin drug levels with warfarin and WELCHOL coadministration in an in vivo study which did not evaluate warfarin pharmacodynamics (INR). [See Post-marketing Experience (6.2)]
c Cyclosporine levels should be monitored and, based on theoretical grounds, cyclosporine should be administered at least 4 hours prior to WELCHOL.
d Patients receiving concomitant metformin ER and colesevelam should be monitored for clinical response as is usual for the use of anti-diabetes drugs.

In an in vivo drug interaction study, WELCHOL and warfarin coadministration had no effect on warfarin drug levels. This study did not assess the effect of WELCHOL and warfarin coadministration on INR. In post-marketing reports, concomitant use of WELCHOL and warfarin has been associated with reduced INR. Therefore, in patients on warfarin therapy, the INR should be monitored before initiating WELCHOL and frequently enough during early WELCHOL therapy to ensure that no significant alteration in INR occurs. Once the INR is stable, continue to monitor the INR at intervals usually recommended for patients on warfarin [See Post-marketing Experience (6.2)].

8 USE IN SPECIFIC POPULATIONS

8.1 Pregnancy

Pregnancy Category B. There are no adequate and well-controlled studies of colesevelam use in pregnant women. Animal reproduction studies in rats and rabbits revealed no evidence of fetal harm. Requirements for vitamins and other nutrients are increased in pregnancy. However, the effect of colesevelam on the absorption of fat-soluble vitamins has not been studied in pregnant women. This drug should be used during pregnancy only if clearly needed.

In animal reproduction studies, colesevelam revealed no evidence of fetal harm when administered to rats and rabbits at doses 50 and 17 times the maximum human dose, respectively. Because animal reproduction studies are not always predictive of human response, this drug should be used in pregnancy only if clearly needed.

8.3 Nursing Mothers

Colesevelam hydrochloride is not expected to be excreted in human milk because colesevelam hydrochloride is not absorbed systemically from the gastrointestinal tract.

8.4 Pediatric Use

The safety and effectiveness of WELCHOL as monotherapy or in combination with a statin were evaluated in children, 10 to 17 years of age with heFH [See Clinical Studies (14.1)]. The adverse reaction profile was similar to that of patients treated with placebo. In this limited controlled study, there were no significant effects on growth, sexual maturation, fat-soluble vitamin levels or clotting factors in the adolescent boys or girls relative to placebo [See Adverse Reactions (6.1)].

Due to tablet size, WELCHOL for Oral Suspension is recommended for use in the pediatric population. Dose adjustments are not required when WELCHOL is administered to children 10 to 17 years of age.

WELCHOL has not been studied in children younger than 10 years of age or in pre-menarchal girls.

8.5 Geriatric Use

Primary Hyperlipidemia: Of the 1350 patients enrolled in the hyperlipidemia clinical studies, 349 (26%) were ≥65 years old, and 58 (4%) were ≥75 years old. No overall differences in safety or effectiveness were observed between these subjects and younger subjects, and other reported clinical experience has not identified differences in responses between the elderly and younger patients, but greater sensitivity of some older individuals cannot be ruled out.

Type 2 Diabetes Mellitus: Of the 2048 patients enrolled in the six diabetes studies, 397 (19%) were ≥65 years old, and 36 (2%) were ≥75 years old. In these trials, WELCHOL 3.8 g/day or placebo was added onto background anti-diabetic therapy. No overall differences in safety or effectiveness were observed between the elderly and younger patients, but greater sensitivity of some older individuals cannot be ruled out.

8.6 Hepatic Impairment

No special considerations or dosage adjustments are recommended when WELCHOL is administered to patients with hepatic impairment.

8.7 Renal Impairment

Type 2 Diabetes Mellitus: Of the 2048 patients enrolled in the six diabetes studies, 807 (39%) had mild renal insufficiency (creatinine clearance [CrCl] 50-<80 mL/min), 61 (3%) had moderate renal insufficiency (CrCl 30-<50 mL/min), and none had severe renal insufficiency (CrCl <30 mL/min), as estimated from baseline serum creatinine using the Modification of Diet in Renal Disease (MDRD) equation. No overall differences in safety or effectiveness were observed between patients with CrCl <50 mL/min (n=53) and those with a CrCl ≥50 mL/min (n=1075) in the add-on to metformin, sulfonylureas, and insulin diabetes studies. In the monotherapy study and add-on to pioglitazone study only 3 and 5 patients respectively had moderate renal insufficiency

10 OVERDOSAGE

Doses of WELCHOL in excess of 4.5 g/day have not been tested. Because WELCHOL is not absorbed, the risk of systemic toxicity is low. However, excessive doses of WELCHOL may cause more severe local gastrointestinal effects (e.g., constipation) than recommended doses.

11 DESCRIPTION

WELCHOL (colesevelam hydrochloride) is a non-absorbed, polymeric, lipid-lowering and glucose-lowering agent intended for oral administration. Colesevelam hydrochloride is a high-capacity bile acid-binding molecule.

Colesevelam hydrochloride is poly(allylamine hydrochloride) cross-linked with epichlorohydrin and alkylated with 1-bromodecane and (6-bromohexyl)-trimethylammonium bromide. The chemical name (IUPAC) of colesevelam hydrochloride is allylamine polymer with 1-chloro-2,3-epoxypropane, [6-(allylamino)-hexyl]trimethylammonium chloride and N-allyldecylamine, hydrochloride. The chemical structure of colesevelam hydrochloride is represented by the following formula:

wherein (a) represents allyl amine monomer units that have not been alkylated by either of the 1-bromodecane or (6-bromohexyl)-trimethylammonium bromide alkylating agents or cross linked by epichlorohydrin; (b) represents allyl amine units that have undergone cross-linking with epichlorohydrin; (c) represents allyl amine units that have been alkylated with a decyl group; (d) represents allyl amine units that have been alkylated with a (6-trimethylammonium) hexyl group, and m represents a number ≥ 100 to indicate an extended polymer network. A small amount of the amines are dialkylated, and are not depicted in the formula above. No regular order of the groups is implied by the structure; cross-linking and alkylation are expected to occur randomly along the polymer chains. A large amount of the amines are protonated. The polymer is depicted in the hydrochloride form; a small amount of the halides are bromide. Colesevelam hydrochloride is hydrophilic and insoluble in water.

WELCHOL Tablets are an off-white, oval, film-coated, solid tablet containing 625 mg colesevelam hydrochloride. In addition, each tablet contains the following inactive ingredients: magnesium stearate, microcrystalline cellulose, silicon dioxide, HPMC (hydroxypropyl methylcellulose), and acetylated monoglyceride. The tablets are imprinted using a water-soluble black ink.

WELCHOL for Oral Suspension is a citrus-flavored, white to pale yellow powder containing yellow granules packaged in single-dose packets containing either 1.875 gram or 3.75 gram colesevelam hydrochloride. In addition, each packet contains the following inactive ingredients: lemon flavor, orange flavor, propylene glycol alginate, simethicone, aspartame, citric acid, medium chain triglycerides, and magnesium trisilicate.

PHENYLKETONURICS: WELCHOL for Oral Suspension contains 13.5 mg phenylalanine per 1.875 gram dose and 27 mg phenylalanine per 3.75 gram dose.

12 CLINICAL PHARMACOLOGY

12.1 Mechanism of Action

Primary Hyperlipidemia: Colesevelam hydrochloride, the active pharmaceutical ingredient in WELCHOL, is a non-absorbed, lipid-lowering polymer that binds bile acids in the intestine, impeding their reabsorption. As the bile acid pool becomes depleted, the hepatic enzyme, cholesterol 7-α-hydroxylase, is upregulated, which increases the conversion of cholesterol to bile acids. This causes an increased demand for cholesterol in the liver cells, resulting in the dual effect of increasing transcription and activity of the cholesterol biosynthetic enzyme, HMG-CoA reductase, and increasing the number of hepatic LDL receptors. These compensatory effects result in increased clearance of LDL-C from the blood, resulting in decreased serum LDL-C levels. Serum TG levels may increase or remain unchanged.

Type 2 Diabetes Mellitus: The mechanism by which WELCHOL improves glycemic control is unknown.

12.2 Pharmacodynamics

A maximum therapeutic response to the lipid-lowering effects of WELCHOL was achieved within 2 weeks and was maintained during long-term therapy. In the diabetes clinical studies, a therapeutic response to WELCHOL, as reflected by a reduction in hemoglobin A1C (A1C), was initially noted following 4-6 weeks of treatment and reached maximal or near maximal effect after 12-18 weeks of treatment.

12.3 Pharmacokinetics

Absorption: Colesevelam hydrochloride is a hydrophilic, water-insoluble polymer that is not hydrolyzed by digestive enzymes and is not absorbed.

Distribution: Colesevelam hydrochloride is not absorbed, and therefore, its distribution is limited to the gastrointestinal tract.

Metabolism: Colesevelam hydrochloride is not metabolized systemically and does not interfere with systemic drug-metabolizing enzymes such as cytochrome P-450.

Excretion: In 16 healthy volunteers, an average of 0.05% of administered radioactivity from a single ^14C-labeled colesevelam hydrochloride dose was excreted in the urine.

Drug Interactions: Drug interactions between colesevelam and concomitantly administered drugs were screened through in vitro studies and confirmed in in vivo studies. In vitro studies demonstrated that cephalexin, metformin, and ciprofloxacin had negligible binding to colesevelam hydrochloride. Therefore, an in vivo pharmacokinetic interaction of WELCHOL with these drugs is unlikely. WELCHOL was found to have no significant effect on the bioavailability of aspirin, atenolol, digoxin, enalapril, fenofibrate, lovastatin, metoprolol, phenytoin, pioglitazone, quinidine, rosiglitazone, sitagliptin, valproic acid, and warfarin. The results of additional in vivo drug interactions of WELCHOL are presented in Table 5.

Table 5 Mean Change in Drug Exposure (AUC0-∞ and Cmax) when Administered with WELCHOL (3.75 g)a
Drug | Dose | Co-administered |  | 1 hr prior to WELCHOL |  | 4 hr prior to WELCHOL
Drug | Dose | AUC0-∞ | Cmax | AUC0-∞ | Cmax | AUC0-∞ | Cmax
Cyclosporine | 200 mg | -34% | -44% | N/A | N/A | N/A | N/A
Ethinyl Estradiol* b | 0.035 mg | -24% | -24% | -18% | -1% | -12% | 0%
Glimepiride b | 4 mg | -18% | -8% | N/A | N/A | -6% | 3%
Glipizide b | 20 mg | -12% | -13% | N/A | N/A | -4% | 0%
Glyburide b | 3 mg | -32% | -47% | -20% | -15% | -7% | 4%
Levothyroxine b | 600 µg | -22% | -33% | 6% | -2% | 1% | 8%
Metformin ER c | 1500 mg | 44% | 8% | N/A | N/A | N/A | N/A
Norethindrone* b | 1 mg | -1% | -20% | 5% | -3% | 6% | 7%
Olmesartan Medoxomilb | 40 mg | -39% | -28% | N/A | N/A | -15% | -4%
Repaglinide | 2 mg | -7% | -19% | -6% | -1% | N/A | N/A
Verapamil sustained- release | 240 mg | -31% | -11% | N/A | N/A | N/A | N/A
a With verapamil, the dose of WELCHOL was 4.5 g
b Should be administered at least 4 hours prior to WELCHOL [See Drug Interactions (7)].
c Patients receiving concomitant metformin ER and colesevelam should be monitored for clinical response as is usual for the use of anti-diabetes drugs [See Drug Interactions (7)].
d Cyclosporine levels should be monitored and, based on theoretical grounds, cyclosporine should be administered at least 4 hours prior to WELCHOL [See Drug Interactions (7)].
* Oral contraceptive containing norethindrone and ethinyl estradiol.
N/A – Not Available

13 NONCLINICAL TOXICOLOGY

13.1 Carcinogenesis, Mutagenesis, Impairment of Fertility

Carcinogenesis: A 104-week carcinogenicity study with colesevelam hydrochloride was conducted in CD-1 mice, at oral dietary doses up to 3 g/kg/day. This dose was approximately 50 times the maximum recommended human dose of 4.5 g/day, based on body weight, mg/kg. There were no significant drug-induced tumor findings in male or female mice. In a 104-week carcinogenicity study with colesevelam hydrochloride in Harlan Sprague-Dawley rats, a statistically significant increase in the incidence of pancreatic acinar cell adenoma was seen in male rats at doses >1.2 g/kg/day (approximately 20 times the maximum human dose, based on body weight, mg/kg) (trend test only). A statistically significant increase in thyroid C-cell adenoma was seen in female rats at 2.4 g/kg/day (approximately 40 times the maximum human dose, based on body weight, mg/kg).

Mutagenesis: Colesevelam hydrochloride and 4 degradants present in the drug substance have been evaluated for mutagenicity in the Ames test and a mammalian chromosomal aberration test. The 4 degradants and an extract of the parent compound did not exhibit genetic toxicity in an in vitro bacterial mutagenesis assay in S. typhimurium and E. coli (Ames assay) with or without rat liver metabolic activation. An extract of the parent compound was positive in the Chinese Hamster Ovary (CHO) cell chromosomal aberration assay in the presence of metabolic activation and negative in the absence of metabolic activation. The results of the CHO cell chromosomal aberration assay with 2 of the 4 degradants, decylamine HCl and aminohexyltrimethyl ammonium chloride HCl, were equivocal in the absence of metabolic activation and negative in the presence of metabolic activation. The other 2 degradants, didecylamine HCl and 6-decylamino-hexyltrimethyl ammonium chloride HCl, were negative in the presence and absence of metabolic activation.

Impairment of Fertility: Colesevelam hydrochloride did not impair fertility in rats at doses up to 3 g/kg/day (approximately 50 times the maximum human dose, based on body weight, mg/kg).

13.2 Animal Toxicology and/or Pharmacology

Reproductive Toxicology Studies

Reproduction studies have been performed in rats and rabbits at doses up to 3 g/kg/day and 1 g/kg/day, respectively (approximately 50 and 17 times the maximum human dose, based on body weight, mg/kg) and have revealed no evidence of harm to the fetus due to colesevelam hydrochloride.

14 CLINICAL STUDIES

14.1 Primary Hyperlipidemia

WELCHOL reduces TC, LDL-C, apolipoprotein B (Apo B), and non-HDL-C when administered alone or in combination with a statin in patients with primary hyperlipidemia.

Approximately 1600 patients were studied in 9 clinical trials with treatment durations ranging from 4 to 50 weeks. With the exception of one open-label, uncontrolled, long term extension study, all studies were multicenter, randomized, double-blind, and placebo controlled. A maximum therapeutic response to WELCHOL was achieved within 2 weeks and was maintained during long-term therapy.

Monotherapy: In a study in patients with LDL-C between 130 mg/dL and 220 mg/dL (mean 158 mg/dL), WELCHOL was given for 24 weeks in divided doses with the morning and evening meals.

As shown in Table 6, the mean LDL-C reductions were 15% and 18% at the 3.8 g and 4.5 g doses. The respective mean TC reductions were 7% and 10%. The mean Apo B reductions were 12% in both treatment groups. WELCHOL at both doses increased HDL-C by 3%. Increases in TG of 9-10% were observed at both WELCHOL doses but the changes were not statistically different from placebo.

Table 6 Response to WELCHOL Monotherapy in a 24-Week Trial Percent Change in Lipid Parameters from Baseline
Grams/Day | N | TC | LDL-C | Apo B | HDL-Ca | Non-HDL-C | TGa
Placebo | 88 | +1 | 0 | 0 | –1 | +1 | +5
3.8 g (6 tablets) | 95 | –7* | –15* | –12* | +3* | –10* | +10
4.5 g (7 tablets) | 94 | –10* | –18* | –12* | +3 | –13* | +9
p<0.05 for lipid parameters compared to placebo, for Apo B compared to baseline.
a Median % change from baseline.

In a study in 98 patients with LDL-C between 145 mg/dL and 250 mg/dL (mean 169 mg/dL), WELCHOL 3.8 g was given for 6 weeks as a single dose with breakfast, as a single dose with dinner, or as divided doses with breakfast and dinner. The mean LDL-C reductions were 18%, 15%, and 18% for the 3 dosing regimens, respectively. The reductions with these 3 regimens were not statistically different from one another.

Combination Therapy: Co-administration of WELCHOL and a statin (atorvastatin, lovastatin, or simvastatin) in 3 clinical studies demonstrated an additive reduction of LDL-C. The mean baseline LDL-C was 184 mg/dL in the atorvastatin study (range 156-236 mg/dL), 171 mg/dL in the lovastatin study (range 115-247 mg/dL), and 188 mg/dL in the simvastatin study (range 148-352 mg/dL). As demonstrated in Table 7, WELCHOL doses of 2.3 g to 3.8 g resulted in an additional 8% to 16% reduction in LDL-C above that seen with the statin alone.

Table 7 Response to WELCHOL in Combination with Atorvastatin, Simvastatin, or Lovastatin Percent Change in Lipid Parameters
Dose/Day | N | TC | LDL-C | Apo B | HDL-Ca | Non-HDL-C | TGa
Atorvastatin Trial (4-week)
Placebo | 19 | +4 | +3 | –3 | +4 | +4 | +10
Atorvastatin 10 mg | 18 | –27* | –38* | –32* | +8 | –35* | –24*
WELCHOL 3.8 g/ Atorvastatin 10 mg | 18 | –31* | –48* | –38* | +11 | –40* | –1
Atorvastatin 80 mg | 20 | –39* | –53* | –46* | +6 | –50* | –33*
Simvastatin Trial (6-week)
Placebo | 33 | –2 | –4 | –4* | –3 | –2 | +6*
Simvastatin 10 mg | 35 | –19* | –26* | –20* | +3* | –24* | –17*
WELCHOL 3.8 g/ Simvastatin 10 mg | 34 | –28* | –42* | –33* | +10* | –37* | –12*
Simvastatin 20 mg | 39 | –23* | –34* | –26* | +7* | –30* | –12*
WELCHOL 2.3 g/ Simvastatin 20 mg | 37 | –29* | –42* | –32* | +4* | –37* | –12*
Lovastatin Trial (4-week)
Placebo | 26 | +1 | 0 | 0 | +1 | +1 | +1
Lovastatin 10 mg | 26 | –14* | –22* | –16* | +5 | –19* | 0
WELCHOL 2.3 g/ Lovastatin 10 mg Together | 27 | –21* | –34* | –24* | +4 | –27* | –1
WELCHOL 2.3 g/ Lovastatin 10 mg | 23 | –21* | –32* | –24* | +2 | –28* | –2
Apart
*p<0.05 for lipid parameters compared to placebo, for Apo B compared to baseline.
aMedian % change from baseline.

In all 3 studies, the LDL-C reduction achieved with the combination of WELCHOL and any given dose of statin therapy was statistically superior to that achieved with WELCHOL or that dose of the statin alone. The LDL-C reduction with atorvastatin 80 mg was not statistically significantly different from the combination of WELCHOL 3.8 g and atorvastatin 10 mg.

The effect of WELCHOL when added to fenofibrate was assessed in 122 patients with mixed hyperlipidemia (Fredrickson Type IIb). Inclusion in the study required LDL-C ≥115 mg/dL and TG 150 mg/dL to 749 mg/dL. Patients were treated with 160 mg of fenofibrate during an 8-week open-label run-in period and then randomly assigned to receive fenofibrate 160 mg plus either WELCHOL 3.8 g or placebo for 6 weeks of double-blind treatment. The overall mean LDL-C at the start of randomized treatment was 144 mg/dL. The results of the study are summarized in Table 8.

Table 8 Response to WELCHOL Added to Fenofibrate in Patients with Mixed Hyperlipidemia (Mean % Change from Treated Baselineb at 6 Weeks)
Treatment | N | TC | LDL-C | Apo B | HDL-C | Non-HDL- C | TGa
Placebo + Fenofibrate 160 mg | 61 | 2 | 2 | 1 | -1 | 2 | -3
WELCHOL + Fenofibrate 160 mg | 61 | -6* | -10* | -7* | -0 | -8* | 6
* p≤0.0002 compared to placebo.
a For triglycerides, median % change from baseline.
b Treated Baseline: following 8-week treatment with open-label fenofibrate 160 mg.

Pediatric Therapy: The safety and efficacy of WELCHOL in pediatric patients were evaluated in an 8-week, multi-center, randomized, double-blind, placebo-controlled, parallel-group study followed by an open-label phase, in 194 boys and postmenarchal girls 10-17 years of age (mean age 14.1 years) with heterozygous familial hypercholesterolemia (heFH), taking a stable dose of an FDA-approved statin (with LDL-C >130 mg/dL) or naïve to lipid lowering therapy (with LDL-C >160 mg/dL). This study had 3 periods: a single-blind, placebo stabilization period; an 8-week, randomized, double-blind, parallel-group, placebo-controlled treatment period; and an 18-week, open-label treatment period. Forty-seven (24%) patients were taking statins and 147 (76%) patients were statin-naïve at screening. The mean baseline LDL-C at Day 1 was approximately 199 mg/dL.

During the double-blind treatment period, patients were assigned randomly to treatment: WELCHOL 3.8 g/day (n=64), WELCHOL 1.9 g/day (n=65), or placebo (n=65). In total, 186 patients completed the double-blind treatment period. After 8 weeks of treatment, WELCHOL 3.8 g/day significantly decreased plasma levels of LDL-C, non-HDL-C, TC, and Apo B and significantly increased HDL-C. A moderate, non-statistically significant increase in TG was observed versus placebo (Table 9).

Table 9 Response to WELCHOL 3.8 g Compared to Placebo in Pediatric Patients 10-17 Years of Age – Mean Percent Change in Lipid Parameters from Baseline to Week 8
Treatment Difference | TC (N=128) | LDL-C (N=128) | Apo B (N=124) | HDL-C (N=128) | Non-HDL- C (N=128) | TGa (N=128)
WELCHOL 3.8 g vs Placebo | -7* | -13* | -8* | +6* | –11* | +5
*p≤0.05 for lipid parameters compared to placebo
Values represent LS mean. Only patients with values at both study baseline and endpoint are included in this table. Study baseline was defined as the last value measured before or on Day 1 prior to the first dose of randomized study medication.
a For triglycerides, median % change from baseline.
Results were based on the ITT population with LOCF

During the open-label treatment period patients were treated with WELCHOL 3.8 g/day. In total, 173 (89%) patients completed 26 weeks of treatment. Results at Week 26 were consistent with those at Week 8.

14.2 Type 2 Diabetes Mellitus

WELCHOL has been studied as monotherapy and in combination with metformin, pioglitazone, sulfonylureas, and insulin. In these studies, WELCHOL and placebo were administered either as 3 tablets twice daily with lunch and dinner or as 6 tablets with dinner alone.

Monotherapy: The efficacy of WELCHOL 3.8 g/day as anti-diabetes monotherapy was evaluated in a randomized double-blind, placebo-controlled trial involving 357 patients (176 WELCHOL and 181 placebo) with T2DM who were treatment-naïve or had not received antihyperglycemic medication within 3 months prior to the start of the study. Statin use at baseline was reported in 13% of the WELCHOL-treated patients and 16% of the placebo-treated patients.

WELCHOL resulted in a statistically significant reduction in A1C of 0.27% compared to placebo (Table 10).

The mean baseline LDL-C was 121 mg/dL in the monotherapy trial. WELCHOL treatment resulted in a placebo-corrected 11% reduction in LDL-C. WELCHOL treatment also reduced serum TC, ApoB, and non-HDL-C (Table 11). The mean change in body weight was -0.6 kg for WELCHOL and -0.7 kg for placebo treatment groups.

Table 10 Glycemic Parameters in a 24-Week Placebo-Controlled Study of WELCHOL Monotherapy in Patients with Type 2 Diabetes
 | WELCHOL 3.8 g/day | Placebo
A1C (%), Mean
N | 175 | 169
Baseline | 8.25 | 8.17
Change from baselinea | -0.26 | 0.01
Treatment difference (p-value) | -0.27 (p=0.013)
FPG (mg/dL), Mean
N | 172 | 166
Baseline | 172 | 168
Change from baselinea | -4.6 | 5.7
Treatment difference (p-value) | -10.3 (p=0.037b)
a Least-squares mean change calculated from an Analysis of Covariance model
bNominal p=value, not controlled for multiplicity testing.
A1C = hemoglobin A1C, FPG = fasting plasma glucose

Table 11 Percent Change in Lipid Parameters in a 24-Week Placebo-Controlled Study of WELCHOL Monotherapy in Patients with Type 2 Diabetes
Dose/Day | N† | TC | LDL-C | Apo B | HDL-C | Non-HDL-C | TGa
WELCHOL 3.8 g | 162 | -3.3* | -10.0* | -5.6* | 1.7 | -4.4* | 15.5
Placebo | 160 | 1.8 | 1.2 | 0.9 | -0.1 | 3.0 | 5.8
*p<0.001 for lipid parameters compared to placebo (this more stringent criterion for statistical significance accounts for multiplicity testing of the lipid parameters, which were secondary endpoints in the diabetes trials)
a Median % change from baseline.
†The number of patients with analyzable data, i.e., a baseline and post-treatment value (last-observation carried forward), varied slightly among different parameters. The N given represents the smallest number of patients included in the analysis for any parameter.

Add-on combination Therapy: The efficacy of WELCHOL 3.8 g/day in patients with type 2 diabetes mellitus was evaluated in 5 double-blind, placebo-controlled add-on therapy trials involving a total of 1691 patients with baseline A1C 7.5-9.5%. Patients were enrolled and maintained on their pre-existing, stable, background anti-diabetic regimen. Statin use at baseline was reported in 41% of the WELCHOL-treated patients and 48% of the placebo-treated patients.

In 3 add-on combination therapy trials (metformin, sulfonylurea and insulin), treatment with WELCHOL resulted in a statistically significant reduction in A1C of 0.5% compared to placebo. Similar placebo-corrected reductions in A1C occurred in patients who received WELCHOL in combination with metformin, sulfonylurea, or insulin monotherapy or combinations of these therapies with other anti-diabetic agents. In the pioglitazone trial, treatment with WELCHOL resulted in a statistically significant reduction in A1C of 0.32% compared to placebo. In the metformin, pioglitazone, and sulfonylurea trials, treatment with WELCHOL also resulted in statistically significant reductions in fasting plasma glucose (FPG) of at least 14 mg/dL compared to placebo.

WELCHOL had consistent effects on A1C across subgroups of age, gender, race, body mass index, and baseline A1C. WELCHOL’s effects on A1C were also similar for the two dosing regimens (3 tablets with lunch and with dinner or 6 tablets with dinner alone).

The mean baseline LDL-C was 104 mg/dL in the metformin study (range 32-214 mg/dL), 107 mg/dL in the pioglitazone study (range 48-263 mg/dL), 106 mg/dL in the sulfonylurea study (range 41-264 mg/dL), 102 mg/dL in the insulin study (range 35-204 mg/dL). In these trials, WELCHOL treatment was associated with a 12% to 16% reduction in LDL-C levels. The percentage decreases in LDL-C were of similar magnitude to those observed in patients with primary hyperlipidemia. WELCHOL treatment was associated with statistically significant increases in TG levels in the studies of patients on insulin, patients on a sulfonylurea, and patients on pioglitazone but not in the study of patients on metformin. The clinical significance of these increases is unknown. WELCHOL is contraindicated in patients with TG levels > 500 mg/dL [See Contraindications (4)] and periodic monitoring of lipid parameters including TG and non-HDL-C levels is recommended [See Warnings and Precautions (5.2) and Adverse Reactions (6.1)].

Body weight did not significantly increase from baseline with WELCHOL therapy, compared with placebo, in any of the add-on combination diabetes studies.

Add-on Combination Therapy with Metformin: WELCHOL 3.8 g/day or placebo was added to background anti-diabetic therapy in a 26-week trial of 316 patients already receiving treatment with metformin alone (N=159) or metformin in combination with other oral agents (N=157). A total of 60% of these patients were receiving ≥1,500 mg/day of metformin. In combination with metformin, WELCHOL resulted in statistically significant placebo-corrected reductions in A1C and FPG (Table 12). WELCHOL also reduced TC, LDL-C, Apo B, and non-HDL-C (Table 13). The mean percent change in serum LDL-C levels with WELCHOL compared to placebo was -16% among statin users and statin non-users; the median percent change in serum TG levels with WELCHOL compared to placebo was -2% among statin users and 10% among statin non-users. The mean change in body weight was -0.5 kg for WELCHOL and -0.3 kg for placebo.

Table 12 Glycemic Parameters in a 26-Week Placebo-Controlled Study of WELCHOL in Combination with Metformin in Patients with Type 2 Diabetes
 | Total Patient Population |  | Metformin Alone |  | Metformin in Combination with Other Oral Anti-Diabetic Agents
 | WELCHOL 3.8 g/day | Placebo | WELCHOL 3.8 g/day | Placebo | WELCHOL 3.8 g/day | Placebo
A1C (%), Mean
N | 148 | 152 | 79 | 76 | 69 | 76
Baseline | 8.1 | 8.1 | 8.2 | 8.2 | 8.1 | 8.0
Change from baselinea | -0.4 | 0.2 | -0.4 | 0.0 | -0.4 | 0.3
Treatment difference (p-value) | -0.5 (p<0.001) |  | -0.5 (p=0.002) |  | -0.6 (p<0.001)
FPG (mg/dL), Mean
N | 149 | 152 | 79 | 76 | 70 | 76
Baseline | 178 | 174 | 184 | 180 | 171 | 168
Change from baselinea | -3 | 11 | -7 | 8 | 0 | 13
Treatment difference (p-value) | -14 (p=0.01) |  | -14 (p=0.07) |  | -14 (p=0.10)
a Least-squares mean change calculated from an Analysis of Covariance model.
A1C = hemoglobin A1C, FPG = fasting plasma glucose

Table 13 Percent Change in Lipid Parameters in a 26-Week Placebo-Controlled Study of WELCHOL in Combination with Metformin in Patients with Type 2 Diabetes
Dose/Day | N† | TC | LDL-C | Apo B | HDL-C | Non-HDL- C | TGa
Total Patient Population
WELCHOL 3.8 g | 125 | -4* | -12* | -4* | 1 | -6* | 12
Placebo | 126 | 3 | 4 | 4 | 0 | 5 | 7
Metformin Alone
WELCHOL 3.8 g | 66 | -3 | -9 | -2 | 1 | -4 | 15
Placebo | 61 | 2 | 0 | 1 | -2 | 4 | 8
Metformin in Combination with Other Oral Anti-diabetic Agents
WELCHOL 3.8 g | 59 | -6* | -15* | -6* | 1 | -7* | 8
Placebo | 65 | 4 | 7 | 7 | 2 | 6 | 5
*p<0.001 for lipid parameters compared to placebo (this more stringent criterion for statistical significance accounts for multiplicity testing of the lipid parameters, which were secondary endpoints in the diabetes trials)
a Median % change from baseline.
†The number of patients with analyzable data, i.e., a baseline and post-treatment value (last-observation carried forward), varied slightly among different parameters. The N given represents the smallest number of patients included in the analysis for any parameter.

Add-on Combination Therapy with pioglitazone: WELCHOL 3.8 g/day or placebo was added to background anti-diabetic therapy in a 24-week trial of 562 patients already receiving treatment with pioglitazone alone (N=51) or pioglitazone in combination with other oral agents (N=511). Of these, most were on dual therapy with metformin (N=298) or triple therapy with metformin and a sulfonylurea (N=139). In combination with pioglitazone-based therapy, WELCHOL resulted in statistically significant reductions in A1C and FPG compared to placebo (Table 14). WELCHOL also reduced TC, LDL-C, Apo B, and non-HDL-C but increased serum TG (Table 15). The mean change in body weight was 0.8 kg for WELCHOL and 0.4 kg for placebo.

Table 14 Glycemic Parameters in a 24-Week Placebo-Controlled Study of WELCHOL in Combination with Pioglitazone Based Therapy in Patients with Type 2 Diabetes
 | WELCHOL 3.8 g/day | Placebo
A1C (%), Mean
N | 271 | 276
Baseline | 8.2 | 8.1
Change from baselinea | -0.34 | -0.02
Treatment difference (p-value) | -0.32 (0.0001)
FPG (mg/dL), Mean
N | 268 | 270
Baseline | 155 | 157
Change from baselinea | -4.8 | +9.9
Treatment difference (p-value) | -14.7 (<0.0001)
a Least-squares mean change calculated from an Analysis of Covariance model.
A1C = hemoglobin A1C, FPG = fasting plasma glucose

Table 15 Percent Change in Lipid Parameters in a 24-Week Placebo-Controlled Study of WELCHOL in Combination with Pioglitazone Based Therapy in Patients with Type 2 Diabetes
Dose/Day | N† | TC | LDL-C | Apo B | HDL-C | Non-HDL- C | TGa
Total Patient Cohort
WELCHOL 3.8 g | 262 | -3* | -9* | -5* | +3 | -5* | +14*
Placebo | 262 | +3 | +7 | +4 | +1 | +5 | +2
*p<0.001 for lipid parameters compared to placebo
a Median % change from baseline
† The N given represents the smallest number of patients included in the analysis for any parameter.

Add-on Combination Therapy with Sulfonylurea: WELCHOL 3.8 g/day or placebo was added to background anti-diabetic therapy in a 26-week trial of 460 patients already treated with sulfonylurea alone (N=156) or sulfonylurea in combination with other oral agents (N=304). A total of 72% of these patients were receiving at least half-maximal doses of sulfonylurea therapy. In combination with a sulfonylurea, WELCHOL resulted in statistically significant placebo-corrected reductions in A1C and FPG (Table 16). WELCHOL also reduced TC, LDL-C, Apo B, and non-HDL-C, but increased serum TG (Table 17). The mean percent change in serum LDL-C levels with WELCHOL compared to placebo was -18% among statin users and -15% among statin non-users; the median percent increase in serum TG with WELCHOL compared to placebo was 29% among statin users and 9% among statin non-users. The mean change in body weight was 0.0 kg for WELCHOL and -0.4 kg for placebo.

Table 16 Glycemic Parameters in a 26-Week Placebo-Controlled Study of WELCHOL in Combination with Sulfonylurea in Patients with Type 2 Diabetes
 | Total Patient Population |  | Sulfonylurea Alone |  | Sulfonylurea in Combination with Other Oral Anti-diabetic Agents
 | WELCHOL 3.8 g/day | Placebo | WELCHOL 3.8 g/day | Placebo | WELCHOL 3.8 g/day | Placebo
A1C (%), Mean
n | 218 | 218 | 69 | 80 | 149 | 138
Baseline | 8.2 | 8.3 | 8.2 | 8.4 | 8.2 | 8.3
Change from baselinea | -0.3 | 0.2 | -0.3 | 0.5 | -0.4 | 0.0
Treatment difference (p-value) | -0.5 (p<0.001) |  | -0.8 (p<0.001) |  | -0.4 (p<0.001)
FPG (mg/dL), Mean
n | 218 | 217 | 70 | 80 | 148 | 137
Baseline | 177 | 181 | 181 | 186 | 175 | 178
Change from baselinea | -4 | 10 | 3 | 15 | -11 | 4
Treatment difference (p-value) | -14 (p=0.009) |  | -12 (p=0.18) |  | -14 (p=0.03)
a Least-squares mean change calculated from an Analysis of Covariance model.
A1C = hemoglobin A1C, FPG = fasting plasma glucose

Table 17 Percent Change in Lipid Parameters in a 26-Week Placebo-Controlled Study of WELCHOL in Combination With Sulfonylurea in Patients with Type 2 Diabetes
Dose/Day | N† | TC | LDL-C | Apo B | HDL-C | Non-HDL- C | TGa
Total Patient Population
WELCHOL 3.8 g | 186 | -5* | -16* | -6* | 1 | -6* | 20*
Placebo | 193 | 0 | 1 | 1 | 0 | 1 | 1
Sulfonylurea Alone
WELCHOL 3.8 g | 57 | -5 | -14* | -5 | -1 | -6 | 17
Placebo | 68 | 0 | 1 | 1 | 1 | 0 | -1
Sulfonylurea in Combination with Other Oral Anti-diabetic Agents
WELCHOL 3.8 g | 129 | -5 | -18* | -7* | 1 | -6 | 21*
Placebo | 125 | 0 | 0 | 1 | 0 | 1 | 2
*p<0.001 for lipid parameters compared to placebo (this more stringent criterion for statistical significance accounts for multiplicity testing of the lipid parameters, which were secondary endpoints in the diabetes trials)
a Median % change from baseline.
† The number of patients with analyzable data, i.e., a baseline and post-treatment value (last-observation carried forward), varied slightly among different parameters. The N given represents the smallest number of patients included in the analysis for any parameter.

Add-on Combination Therapy with Insulin: WELCHOL 3.8 g/day or placebo was added to background anti-diabetic therapy in a 16-week trial of 287 patients already treated with insulin alone (N=116) or insulin in combination with oral agents (N=171). At baseline, the median daily insulin dose was 70 units in the WELCHOL group and 65 units in the placebo group. In combination with insulin, WELCHOL resulted in a statistically significant placebo-corrected reduction in A1C (Table 18). WELCHOL also reduced LDL-C and Apo B, but increased serum TG (Table 19). The mean percent change in serum LDL-C levels with WELCHOL compared to placebo was -13% among statin users and statin non-users; the median percent increase in serum TG levels with WELCHOL compared to placebo was 24% among statin users and 17% among statin non-users. The mean change in body weight was 0.6 kg for WELCHOL and 0.2 kg for placebo.

Table 18 Glycemic Parameters in a 16-Week Placebo-Controlled Study of WELCHOL in Combination with Insulin in Patients with Type 2 Diabetes
 | Total Patient Population |  | Insulin Alone |  | Insulin in Combination with Oral Anti-diabetic Agents
 | WELCHOL 3.8 g/day | Placebo | WELCHOL 3.8 g/day | Placebo | WELCHOL 3.8 g/day | Placebo
A1C (%), Mean
n | 144 | 136 | 54 | 55 | 90 | 81
Baseline | 8.3 | 8.2 | 8.2 | 8.3 | 8.3 | 8.2
Change from baselinea | -0.4 | 0.1 | -0.4 | 0.2 | -0.4 | 0.0
Treatment difference (p-value) | -0.5 (p<0.001) |  | -0.6 (p<0.001) |  | -0.4 (p<0.001)
FPG (mg/dL), Mean
n | 144 | 136 | 54 | 55 | 90 | 81
Baseline | 165 | 151 | 165 | 163 | 165 | 143
Change from baselinea | 2 | 16 | 8 | 17 | -4 | 14
Treatment difference (p-value) | -15 (p=0.08) |  | -9 (p=0.51) |  | -18 (p=0.09)
a Least-squares mean change calculated from an Analysis of Covariance model.
A1C = hemoglobin A1C, FPG = fasting plasma glucose

Table 19 Percent Change in Lipid Parameters in a 16-Week Placebo-Controlled Study of WELCHOL in Combination with Insulin in Patients with Type 2 Diabetes
Dose/Day | N† | TC | LDL-C | Apo B | HDL-C | Non-HDL- C | TGa
Total Patient Population
WELCHOL 3.8 g | 129 | -3 | -12* | -4 | -1 | -3 | 23*
Placebo | 121 | 1 | 1 | 1 | 0 | 1 | 0
Insulin Alone
WELCHOL 3.8 g | 46 | -3 | -12 | -5 | 0 | -3 | 19
Placebo | 48 | 2 | 4 | 2 | 3 | 2 | -2
Insulin in Combination with Oral Anti-diabetic Agents
WELCHOL 3.8 g | 83 | -4 | -13 | -4 | -1 | -3 | 25*
Placebo | 73 | -1 | -3 | 0 | -1 | -1 | 2
*p<0.001 for lipid parameters compared to placebo (this more stringent criterion for statistical significance accounts for multiplicity testing of the lipid parameters, which were secondary endpoints in the diabetes trials)
a Median % change from baseline.
† The number of patients with analyzable data, i.e., a baseline and post-treatment value (last-observation carried forward), varied slightly among different parameters. The N given represents the smallest number of patients included in the analysis for any parameter.

HOW SUPPLIED

Product: 68151-4362

NDC: 68151-4362-1 1 TABLET, FILM COATED in a PACKAGE

17 PATIENT COUNSELING INFORMATION

Dosing: Patients should be advised to take WELCHOL Tablets with a meal and liquid. WELCHOL can be taken as 6 tablets once daily or 3 tablets twice daily. Patients should be advised to take WELCHOL for Oral Suspension as one 3.75 gram packet once daily or one 1.875 gram packet twice daily. To prepare, empty the entire contents of one packet into a glass or cup. Add ½ to 1 cup (4 to 8 ounces) of water, fruit juice, or diet soft drinks. Stir well and drink. WELCHOL for Oral Suspension should be taken with meals. To avoid esophageal distress, WELCHOL for Oral Suspension should not be taken in its dry form. Always mix WELCHOL for Oral Suspension with water, fruit juice, or diet soft drinks before ingesting [See Dosage and Administration (2)].

Drug interactions: Drugs with a known interaction with colesevelam (e.g., cyclosporine, glimepiride, glipizide, glyburide, levothyroxine, olmesartan medoxomil, oral contraceptives) should be administered at least 4 hours prior to WELCHOL. In an in vivo drug interaction study, there was no significant effect on the bioavailability of phenytoin; however, due to its narrow therapeutic index and post-marketing reports consistent with potential drug-drug interactions, phenytoin should be administered at least 4 hours prior to WELCHOL. Drugs that have not been tested for interaction with colesevelam, especially those with a narrow therapeutic index, should also be administered at least 4 hours prior to WELCHOL. Alternatively the physician should monitor blood levels of the coadministered drug. Patients receiving concomitant metformin ER and colesevelam should be monitored for clinical response as is usual for the use of anti-diabetes drugs [See Drug Interactions (7)].

Gastrointestinal: WELCHOL can cause constipation. WELCHOL is contraindicated in patients with a history of bowel obstruction. WELCHOL is not recommended in patients who may be at risk of bowel obstruction, including patients with gastroparesis, other gastrointestinal motility disorders, or a history of major gastrointestinal surgery. Patients should be instructed to consume a diet that promotes bowel regularity. Patients should be instructed to promptly discontinue WELCHOL and seek medical attention if severe abdominal pain or severe constipation occurs. Because of the tablet size, WELCHOL Tablets can cause dysphagia or esophageal obstruction and should be used with caution in patients with dysphagia or swallowing disorders. To avoid esophageal distress, WELCHOL for Oral Suspension should not be taken in its dry form. Always mix WELCHOL for Oral Suspension with water, fruit juice, or diet soft drinks before ingesting [See Warnings and Precautions (5.4)].

Hypertriglyceridemia and pancreatitis: Patients should be instructed to discontinue WELCHOL and seek prompt medical attention if the hallmark symptoms of acute pancreatitis occur (e.g., severe abdominal pain with or without nausea and vomiting) [See Warnings and Precautions (5.2)].

17.1 Primary Hyperlipidemia:

Patients should be advised to adhere to their National Cholesterol Education Program (NCEP)-recommended diet.

17.2 Type 2 Diabetes Mellitus:

General: Patients should be advised that it is important to adhere to dietary instructions, a regular exercise program, and regular testing of blood glucose.

Hypertriglyceridemia and cardiovascular disease: Patients should be informed that WELCHOL may increase serum triglyceride concentrations and that the long-term effect of hypertriglyceridemia on the risk of coronary artery disease is uncertain [See Warnings and Precautions (5.2)].

Marketed by: | Daiichi Sankyo, Inc. Parsippany, New Jersey 07054
Active Ingredient: | Product of Austria